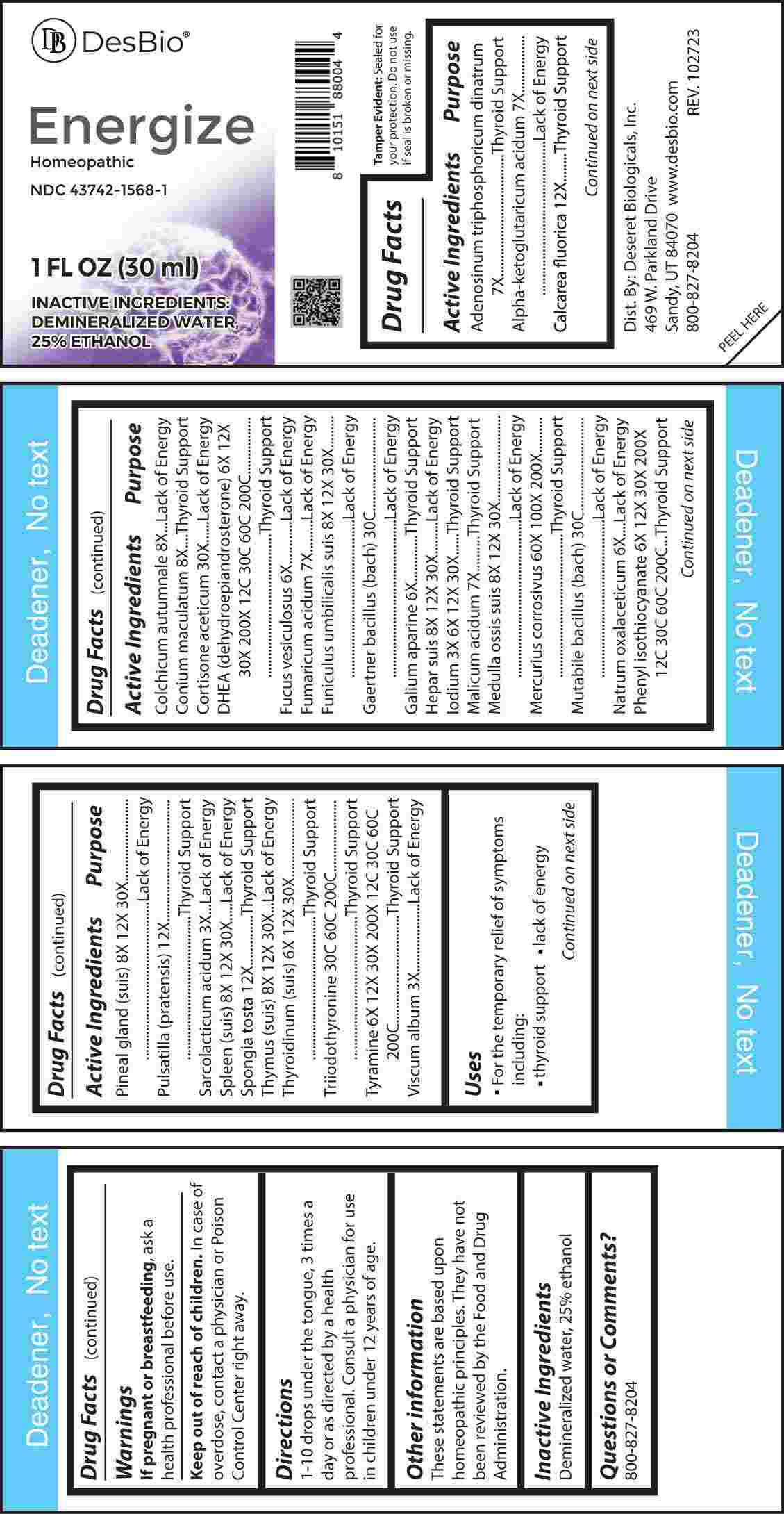 DRUG LABEL: Energize
NDC: 43742-1568 | Form: LIQUID
Manufacturer: Deseret Biologicals, Inc.
Category: homeopathic | Type: HUMAN OTC DRUG LABEL
Date: 20240219

ACTIVE INGREDIENTS: LACTIC ACID, L- 3 [hp_X]/1 mL; VISCUM ALBUM FRUITING TOP 3 [hp_X]/1 mL; IODINE 3 [hp_X]/1 mL; FUCUS VESICULOSUS 6 [hp_X]/1 mL; GALIUM APARINE WHOLE 6 [hp_X]/1 mL; SODIUM DIETHYL OXALACETATE 6 [hp_X]/1 mL; THYROID 6 [hp_X]/1 mL; PRASTERONE 6 [hp_X]/1 mL; PHENYL ISOTHIOCYANATE 6 [hp_X]/1 mL; TYRAMINE 6 [hp_X]/1 mL; ADENOSINE TRIPHOSPHATE DISODIUM 7 [hp_X]/1 mL; .ALPHA.-KETOGLUTARIC ACID 7 [hp_X]/1 mL; FUMARIC ACID 7 [hp_X]/1 mL; MALIC ACID 7 [hp_X]/1 mL; COLCHICUM AUTUMNALE BULB 8 [hp_X]/1 mL; CONIUM MACULATUM FLOWERING TOP 8 [hp_X]/1 mL; SUS SCROFA UMBILICAL CORD 8 [hp_X]/1 mL; PORK LIVER 8 [hp_X]/1 mL; SUS SCROFA BONE MARROW 8 [hp_X]/1 mL; SUS SCROFA PINEAL GLAND 8 [hp_X]/1 mL; SUS SCROFA SPLEEN 8 [hp_X]/1 mL; SUS SCROFA THYMUS 8 [hp_X]/1 mL; CALCIUM FLUORIDE 12 [hp_X]/1 mL; PULSATILLA PRATENSIS WHOLE 12 [hp_X]/1 mL; SPONGIA OFFICINALIS SKELETON, ROASTED 12 [hp_X]/1 mL; CORTISONE ACETATE 30 [hp_X]/1 mL; MERCURIC CHLORIDE 60 [hp_X]/1 mL; SALMONELLA ENTERICA SUBSP. ENTERICA SEROVAR ENTERITIDIS 30 [hp_C]/1 mL; ESCHERICHIA COLI 30 [hp_C]/1 mL; LIOTHYRONINE 30 [hp_C]/1 mL
INACTIVE INGREDIENTS: WATER; ALCOHOL

DRUG FACTS:

ACTIVE INGREDIENTS:

Adenosinum Triphosphoricum Dinatrum 7X, Alpha-Ketoglutaricum Acidum 7X, Calcarea Fluorica 12X, Colchicum Autumnale 8X, Conium Maculatum 8X, Cortisone Aceticum 30X, DHEA (Dehydroepiandrosterone) 6X, 12X, 30X, 200X, 12C, 30C, 60C, 200C, Fucus Vesiculosus 6X, Fumaricum Acidum 7X, Funiculus Umbilicalis Suis 8X, 12X, 30X, Gaertner Bacillus (Bach) 30C, Galium Aparine 6X, Hepar Suis 8X, 12X, 30X, Iodium 3X, 6X, 12X, 30X, Malicum Acidum 7X, Medulla Ossis Suis 8X, 12X, 30X, Mercurius Corrosivus 60X, 100X, 200X, Mutabile Bacillus (Bach) 30C, Natrum Oxalaceticum 6X, Phenyl Isothiocyanate 6X, 12X, 30X, 200X, 12C, 30C, 60C, 200C, Pineal Gland (Suis) 8X, 12X, 30X, Pulsatilla (Pratensis) 12X, Sarcolacticum Acidum 3X, Spleen (Suis) 8X, 12X, 30X, Spongia Tosta 12X, Thymus (Suis) 8X, 12X, 30X, Thyroidinum (Suis) 6X, 12X, 30X, Tri-Iodothyronine 30C, 60C, 200C, Tyramine 6X, 12X, 30X, 200X, 12C, 30C, 60C, 200C, Viscum Album 3X.

PURPOSE:

Adenosinum Triphosphoricum Dinatrum – Thyroid Support, Alpha-Ketoglutaricum Acidum – Lack of Energy, Calcarea Fluorica – Thyroid Support, Colchicum Autumnale – Lack of Energy, Conium Maculatum – Thyroid Support, Cortisone Aceticum – Lack of Energy, DHEA (Dehydroepiandrosterone) – Thyroid Support, Fucus Vesiculosus – Lack of Energy, Fumaricum Acidum – Lack of Energy, Funiculus Umbilicalis Suis – Lack of Energy, Gaertner Bacillus (Bach) – Lack of Energy, Galium Aparine – Thyroid Support, Hepar Suis – Lack of Energy, Iodium – Thyroid Support, Malicum Acidum – Thyroid Support, Medulla Ossis Suis – Lack of Energy, Mercurius Corrosivus – Thyroid Support, Mutabile Bacillus (Bach) – Lack of Energy, Natrum Oxalaceticum – Lack of Energy, Phenyl Isothiocyanate – Thyroid Support, Pineal Gland (Suis) – Lack of Energy, Pulsatilla (Pratensis) – Thyroid Support, Sarcolacticum Acidum – Lack of Energy, Spleen (Suis) – Lack of Energy, Spongia Tosta – Thyroid Support, Thymus (Suis) – Lack of Energy, Thyroidinum (Suis) – Thyroid Support, Tri-Iodothyronine – Thyroid Support, Tyramine – Thyroid Support, Viscum Album – Lack of Energy.

USES:

• For the temporary relief of symptoms including:

• thyroid support • lack of energy

These statements are based upon homeopathic principles. They have not been reviewed by the Food and Drug Administration.

WARNINGS:

If pregnant or breast-feeding, ask a health professional before use.

Keep out of reach of children. In case of overdose, contact a physician or Poison Control Center right away.

Tamper Evident: Sealed for your protection. Do not use if seal is broken or missing.

KEEP OUT OF REACH OF CHILDREN:

In case of overdose, contact a physician or Poison Control Center right away.

DIRECTIONS:

1-10 drops under the tongue, 3 times a day or as directed by a health professional. Consult a physician for use in children under 12 years of age.

INACTIVE INGREDIENTS:

Demineralized water, 25% ethanol

QUESTIONS:

Dist. By: Deseret Biologicals, Inc.

469 W. Parkland Drive

Sandy, UT 84070

www.desbio.com

800-827-8204

PACKAGE LABEL DISPLAY:

Des Bio

Energize

Homeopathic

NDC 43742-1568-1

1 FL OZ (30 ml)